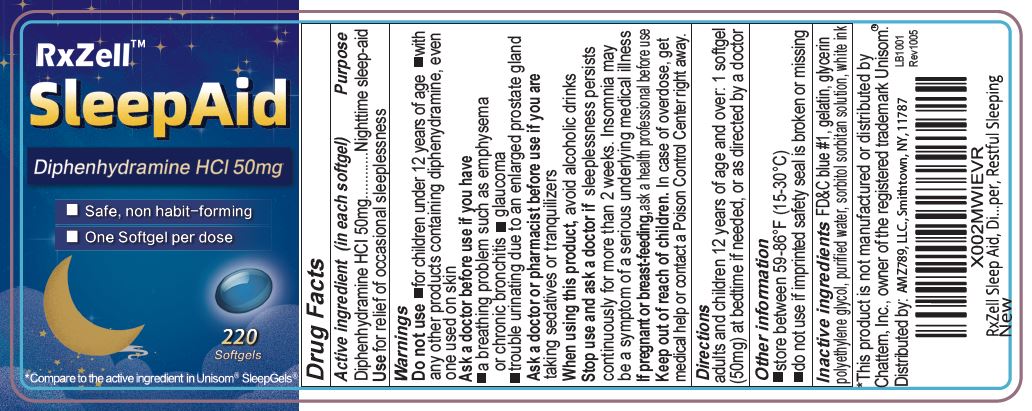 DRUG LABEL: DIPHENHYDRAMINE HYDROCHLORIDE 50mg
NDC: 73629-001 | Form: CAPSULE, LIQUID FILLED
Manufacturer: AMZ789 LLC
Category: otc | Type: HUMAN OTC DRUG LABEL
Date: 20260107

ACTIVE INGREDIENTS: DIPHENHYDRAMINE HYDROCHLORIDE 50 mg/1 1
INACTIVE INGREDIENTS: POLYETHYLENE GLYCOL, UNSPECIFIED; WATER; SORBITOL; GLYCERIN; GELATIN; FD&C BLUE NO. 1

diphenhydramine HCl 50mg softgels

ACTIVE INGREDIENT

Diphenhydramine HCl 50mg

DOSAGE AND ADMINISTRATION

Dipheyhydramine HCl 50mg

Use

For relief of occasional sleeplessness

INDICATIONS AND USAGE

for relied of occasional sleeplessness

Warnings

DO NOT USE

for children under 12 years of age

with any other products containing diphenhydramine, even one used on skin

Ask a doctor or pharmacist before use if

you have a breathing problem such as emphysema or chronic bronchitis, glaucoma, trouble urinating due to an enlarged prostate gland

you are taking sedatives or tranquilizers

When using this product

avoid alcholic drinks

Stop use and ask a doctor if

sleeplessness presists continuously for more than 2 weeks. Insomnic may be a symptom of a series underlying medical illness

If pregnant or breast-feeding

ask a health professional before use

KEEP OUT OF REACH OF CHILDREN

In case of overdose, get medical help or contact a Poison Control Center right away (1-800-222-1222)

Direction

adults and children 12 years and over: 1 softgel at bedtime if needed, or as directed by a doctor

INACTIVE INGREDIENT

FD&C blue #1, gelatin, glycerin, polyethylene glycol, purified water, sorbitol sorbitan solution, white ink

PACKAGE LABEL

RxZell

SleepAid

Dyphenhydramine HCl 50mg

Non Habit-Forming

Easy to Swallow